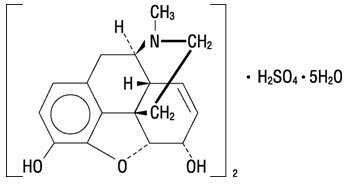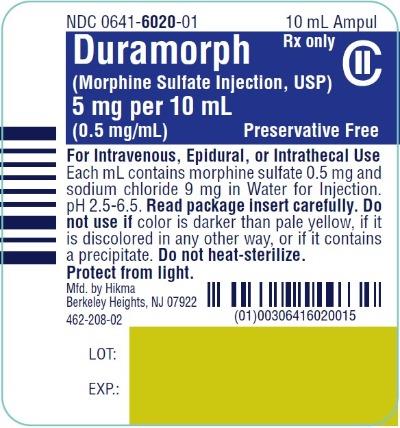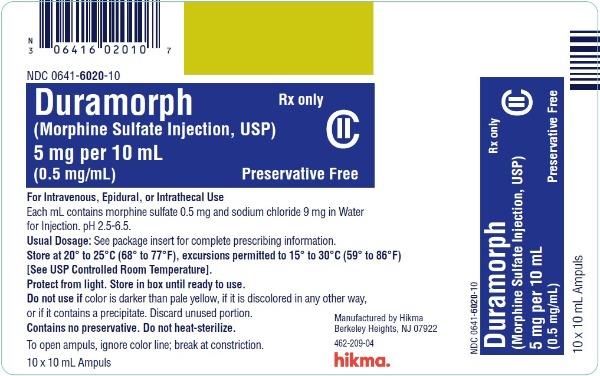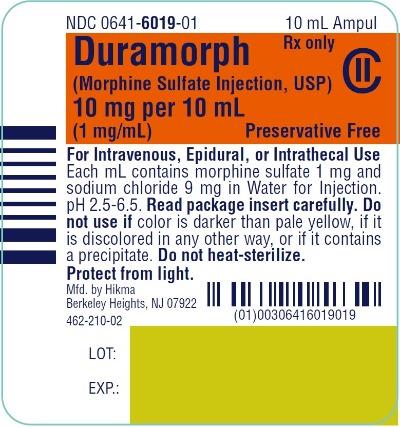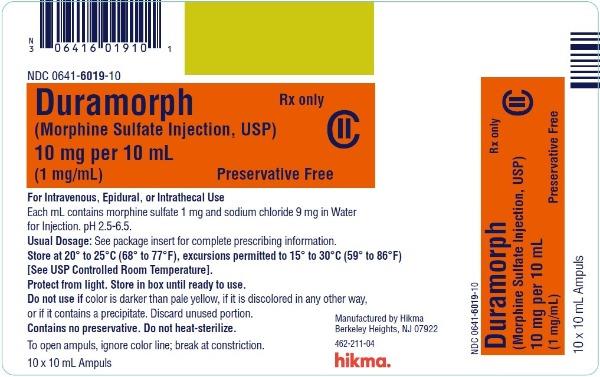 DRUG LABEL: Duramorph
NDC: 0641-6020 | Form: INJECTION
Manufacturer: Hikma Pharmaceuticals USA Inc.
Category: prescription | Type: HUMAN PRESCRIPTION DRUG LABEL
Date: 20251231
DEA Schedule: CII

ACTIVE INGREDIENTS: MORPHINE SULFATE 0.5 mg/1 mL
INACTIVE INGREDIENTS: SODIUM CHLORIDE 9 mg/1 mL; WATER

HIGHLIGHTS OF PRESCRIBING INFORMATION

These highlights do not include all the information needed to use DURAMORPH safely and effectively. See full prescribing information for DURAMORPH.
DURAMORPH (morphine sulfate injection), for intravenous, epidural, or intrathecal use, CII
Initial U.S. Approval: 1941

WARNING: SERIOUS AND LIFE-THREATENING RISKS FROM USE OF DURAMORPH

See full prescribing information for complete boxed warning.

- Single-dose neuraxial administration may result in acute or delayed respiratory depression up to 24 hours. Because of the risk of severe adverse reactions when DURAMORPH is administered by the epidural or intrathecal route of administration, patients must be observed in a fully equippedandstaffedenvironmentforatleast24hoursafter the initial dose. (5.1)
- DURAMORPH exposes users to risks of opioid addiction, abuse, and misuse, which can lead to overdose and death. Assess patient’s risk before prescribing and reassess regularly for these behaviors and conditions. (5.2)
- Serious, life-threatening, or fatal respiratory depression may occur with use of DURAMORPH, especially during initiation or following a dosage increase. To reduce the risk of respiratory depression, proper dosing and titration of DURAMORPH are essential. (5.3)
- Concomitant use of opioids with benzodiazepines or other central nervous system (CNS) depressants, including alcohol, may result in profound sedation, respiratory depression, coma, and death. Reserve concomitant prescribing for use in patients for whom alternative treatment options are inadequate. (5.4, 7)
- Advise pregnant women using opioids for an extended period of time of the risk of Neonatal Opioid Withdrawal Syndrome, which may be life-threatening if not recognized and treated. Ensure that management by neonatology experts will be available at delivery (5.5)

RECENT MAJOR CHANGES

Boxed Warning 12/2025

Indications and Usage (1) 12/2025

Dosage and Administration (2.1, 2.6) 12/2025

Warnings and Precautions (5.2, 5.3, 5.4, 5.14, 5.16) 12/2025

1 INDICATIONS AND USAGE

DURAMORPH is an opioid agonist, indicated for:

1. the management of pain severe enough to require use of an opioid analgesic by intravenous administration and for which alternative treatments are not expected to be adequate.
2. the epidural or intrathecal management of pain without attendant loss of motor, sensory, or sympathetic function. (1)

Limitation of Use

DURAMORPH is not for use in Continuous Microinfusion Devices.

Because of the risks of addiction, abuse, misuse, overdose, and death, which can occur at any dosage or duration, and persist over the course of therapy, reserve opioid analgesics, including DURAMORPH for use in patients for whom alternative treatment options are ineffective, not tolerated or would be otherwise inadequate to provide sufficient management of pain. (1, 5.2)

2 DOSAGE AND ADMINISTRATION

- DURAMORPH should be prescribed only by healthcare professionals who are knowledgeable about the use of opioids and how to mitigate the associated risks. (2.1)

- Should be administered by or under the direction of a physician experienced in the techniques of epidural or intrathecal administration. (2.1)
- Use the lowest effective dosage for the shortest duration of time consistent with individual patient treatment goals. Reserve titration to higher doses of DURAMORPH for patients in whom lower doses are insufficiently effective and in whom the expected benefits of using a higher dose opioid clearly outweigh the substantial risks. (2.2, 5)
- Initiate the dosing regimen for each patient individually, taking into account the patient’s underlying cause and severity of pain, prior analgesic treatment and response, and risk factors for addiction, abuse, and misuse. (2.1, 5.2)
- Respiratory depression can occur at any time during opioid therapy, especially when initiating and following dosage increases with DURAMORPH. Consider this risk when selecting an initial dose and when making dose adjustments. (2, 5.3)
- Dosage for Intravenous Administration: 2 mg to 10 mg/70 kg of body weight. (2.3)
- Dosage for Epidural Administration: Initial injection of 5 mg in the lumbar region may provide satisfactory pain relief for up to 24 hours. If adequate pain relief is not achieved within one hour, carefully administer incremental doses of 1 to 2 mg at intervals sufficient to assess effectiveness. Administer no more than 10 mg/24 hr. (2.4)
- Dosage for Intrathecal Administration: A single injection of 0.2 to 1 mgmayprovidesatisfactorypainreliefforupto24hours.Repeated intrathecal injections of DURAMORPH are not recommended. (2.5)
- Periodically reassess patients receiving DURAMORPH to evaluate the continued need for opioid analgesics to maintain pain control, for the signs or symptoms of adverse reactions, and the development of addiction, abuse or misuse.(2.6)
- Do not rapidly reduce or abruptly discontinue DURAMORPH abruptly in a physically-dependent patient. (2.6, 5.16)

3 DOSAGE FORMS AND STRENGTHS

Injection: 5 mg/10 mL (0.5 mg/mL) Preservative-free amber glass ampuls
Injection: 10 mg/10 mL (1 mg/mL) Preservative-free amber glass ampuls (3)

4 CONTRAINDICATIONS

DURAMORPH is contraindicated in patients with:

- Significant respiratory depression (4)
- Acute or severe bronchial asthma in an unmonitored setting in absence of resuscitative equipment (4)
- Concurrent use of monoamine oxidase inhibitors (MAOIs) or use of MAOIs within the last 14 days (4)
- Known or suspected gastrointestinal obstruction, including paralytic ileus (4)
- Hypersensitivity or intolerance to morphine (4)

Neuraxial administration of DURAMORPH is contraindicated in patients with:

- Infection at the injection microinfusion site (4)
- Concomitant anticoagulant therapy (4)
- Uncontrolled bleeding diathesis (4)
- The presence of any other concomitant therapy or medical condition which would render epidural or intrathecal administration of medication especially hazardous. (4)

5 WARNINGS AND PRECAUTIONS

- Risk of Tolerance and Myoclonic Activity: Monitor patients for unusual acceleration of neuraxial morphine, which may cause myoclonic-like spasm of lower extremities. Detoxification maybe required. (5.6)
- Chest Wall Rigidity: Rapid intravenous administration may result in chest wall rigidity. (5.7)
- Opioid Induced Hyperalgesia and Allodynia: Opioid Induced Hyperalgesia (OIH) occurs when an opioid analgesic paradoxically causes an increase in pain, or an increase in sensitivity to pain. If a patient is suspected to be experiencing OIH, carefully consider appropriately decreasing the dose of the current opioid analgesic, or opioid rotation (safety switching the patient to a different opioid moiety). (5.8)
- Life-Threatening Respiratory Depression in Patients with Chronic Pulmonary Disease or in Elderly, Cachectic, or Debilitated Patients: Monitor closely, particularly during initiation and titration. (5.9)
- Adrenal Insufficiency: If diagnosed, treat with physiologic replacement of corticosteroids, and wean patient off of the opioid. (5.11)
- Severe Hypotension: Monitor during dosage initiation and titration. AvoiduseofDURAMORPHinpatientswithcirculatoryshock.(5.12)
- Risks of Use in Patients with Increased Intracranial Pressure, Brain Tumors, Head Injury, or Impaired Consciousness: Monitor for sedation and respiratory depression. Avoid use of DURAMORPH in patients with impaired consciousness or coma. (5.13)

6 ADVERSE REACTIONS

Most serious adverse reactions were respiratory depression and/or respiratory arrest. (6)

To report SUSPECTED ADVERSE REACTIONS, contact Hikma Pharmaceuticals USA Inc. at 1-877-845-0689 or FDA at 1-800-FDA-1088 or www.fda.gov/medwatch.

7 DRUG INTERACTIONS

- Serotonergic Drugs: Concomitant use may result in serotonin syndrome. Discontinue DURAMORPH if serotonin syndrome is suspected. (7)
- Mixed Agonist/Antagonist and Partial Agonist Opioid Analgesics: Avoid use with DURAMORPH because they may reduce the analgesic effect of DURAMORPH or precipitate withdrawal symptoms. (7)

8 USE IN SPECIFIC POPULATIONS

- Pregnancy: May cause fetal harm. (8.1)

FULL PRESCRIBING INFORMATION

WARNING: SERIOUS AND LIFE-THREATENING RISKS FROM USE OF DURAMORPH

Risks with Neuraxial Administration

Single-dose neuraxial administration may result in acute or delayed respiratory depression up to 24 hours. Because of the risk of severe adverse reactions when DURAMORPH is administered by the epidural or intrathecal route of administration, patients must be observed in a fully equipped and staffed environment for at least 24 hours after the initial dose [see Warnings and Precautions (5.1)].

Addiction, Abuse, and Misuse

Because the use of DURAMORPH exposes patients and other users to the risks of opioid addiction, abuse, and misuse, which can lead to overdose and death, assess each patient’s risk prior to prescribing and reassess all patients regularly for the development of these behaviors and conditions [see Warnings and Precautions (5.2)].

Life-Threatening Respiratory Depression

Serious, life-threatening, or fatal respiratory depression may occur with use of DURAMORPH, especially during initiation or following a dosage increase. To reduce the risk of respiratory depression, proper dosing and titration of DURAMORPH are essential [see Warnings and Precautions (5.3)].

Risks From Concomitant Use With Benzodiazepines Or Other CNS Depressants

Concomitant use of opioids with benzodiazepines or other central nervous system (CNS) depressants, including alcohol, may result in profound sedation, respiratory depression, coma, and death. Reserve concomitant prescribing of DURAMORPH and benzodiazepines or other CNS depressants for use in patients for whom alternative treatment options are inadequate [see Warnings and Precautions (5.4), Drug Interactions (7)].

Neonatal Opioid Withdrawal Syndrome (NOWS)

Advise pregnant women using opioids for an extended period of time of the risk of Neonatal Opioid Withdrawal Syndrome, which may be life threatening if not recognized and treated. Ensure that management by neonatology experts will be available at delivery [see Warnings and Precautions (5.5)].

1 INDICATIONS AND USAGE

DURAMORPH is indicated for:

- the management of pain severe enough to require use of an opioid analgesic by intravenous administration, and for which alternative treatments are not expected to be adequate.
- the epidural or intrathecal management of pain without attendant loss of motor, sensory, or sympathetic function.

Limitation of Use

DURAMORPH is not for use in continuous microinfusion devices.

Because of the risks of addiction, abuse, misuse, overdose, and death, which can occur at any dosage or duration and persist over the course of therapy [see Warnings and Precautions (5.2)], reserve opioid analgesiscs, including DURAMORPH for use in patients for whom alternative treatment options are ineffective, not tolerated or would be otherwise inadequate to provide sufficient management of pain.

2 DOSAGE AND ADMINISTRATION

2.1 Important Dosage and Administration Instructions

Do Not Use DURAMORPH in Continuous Microinfusion Devices.

DURAMORPH should be administered by or under the direction of a physician experienced in the techniques of epidural or intrathecal administration and familiar with the patient management problems associated with epidural or intrathecal drug administration and the labeling, and should take place only in settings where adequate patient monitoring is possible.

- DURAMORPHshouldbeprescribedonlybyhealthcareprofessionalswhoareknowledgeable about the use of opioids and how to mitigate the associated risks.
- Because of the risk of delayed respiratory depression, patients should be observed in a fully equipped and staffed environment for at least 24 hours. Respiratory depression (both early and late onset)hasoccurredmorefrequentlyfollowingintrathecaladministrationthanepidural administration.
- Becauseepiduraladministrationhasbeenassociatedwithlesspotentialforimmediateorlate adverse effects than intrathecal administration, the epidural route should be used whenever possible.
- Forsafetyreasons,itisrecommendedthatadministrationofDURAMORPHbytheepiduralor intrathecal routes be limited to the lumbar area.
- Have resuscitative equipment and an opioid overdose reversal agent (e.g., naloxone, nalmefene) immediately available for the management of respiratory depression as well as complicationswhichmightresultfrominadvertentintrathecalorintravascularinjection(note: intrathecal dosage is usually 1/10 that of epidural dosage).

Epidural Administration

Verify proper placement of a needle or catheter in the epidural space before DURAMORPH is injected.

Acceptable techniques for verifying proper placement include: a) aspiration to check for absence of blood or cerebrospinal fluid, or b) administration of 5 mL (3 mL in obstetric patients) of 1.5% PRESERVATIVE-FREE Lidocaine and Epinephrine (1:200,000) Injection and then observe the patient for lack of tachycardia (this indicates that vascular injection has not been made) and lack of sudden onset of segmental anesthesia (this indicates that intrathecal injection has not been made).

Safety and Handling Instructions:

DURAMORPH is supplied in sealed ampuls. Accidental dermal exposure should be treated by the removal of any contaminated clothing and rinsing the affected area with water.

Inspect parenteral drug products for particulate matter and discoloration prior to administration, whenever solution and container permit. Do not use if color is darker than pale yellow, if it is discolored in any other way, or if it contains a precipitate.

DURAMORPH is intended for single use only. Protect from light, discard any unused portion. Do not heat-sterilize.

2.2 Initial Dosage

The starting dose of DURAMORPH must be individualized.

- Use the lowest effective dosage for the shortest duration of time consistent with individual patient treatment goals [see Warnings and Precautions (5)]. Because the risk of overdose increases as opioid doses increase, reserve titration to higher doses of DURAMORPH for patients in whom lower doses are insufficiently effective and in whom the expected benefits of using a higher dose opioid clearly outweigh the substantial risks.
- Many acute pain conditions (e.g., the pain that occurs with a number of surgical procedures or acute musculoskeletal injuries) require no more than a few days of an opioid analgesic. Clinical guidelines on opioid prescribing for some acute pain conditions are available.
- There is variability in the opioid analgesic dose and duration needed to adequately manage pain due both to the cause of pain and to individual patient factors. Initiate the dosing regimen for each patient individually, taking into account the patient’s underlying cause and severity of pain, prior analgesic treatment and response, and risk factors for addiction, abuse, and misuse [see Warnings and Precautions (5.2)].
- Respiratory depression can occur at any time during opioid therapy, especially when initiating and following dosage increases with DURAMORPH. Consider this risk when selecting an initial dose and when making dose adjustments [see Warnings and Precautions (5)].

2.3 Dosage for Intravenous Administration

Adult Dosage: The initial dose of morphine should be 2 mg to 10 mg/70 kg of body weight, and at the lowest dose necessary to achieve adequate analgesia. Titrate the dose based upon the individual patient’s response to their initial dose of DURAMORPH

2.4 Dosage for Epidural Administration

Adult Dosage: Initial injection of 5 mg in the lumbar region may provide satisfactory pain relief for up to 24 hours. If adequate pain relief is not achieved within one hour, careful administration of incremental doses of 1 to 2 mg at intervals sufficient to assess effectiveness may be given. Do not administer more than 10 mg per 24 hours.

2.5 Dosage for Intrathecal Administration

Adult Dosage: Intrathecal dosage is usually 1/10 that of epidural dosage. A single injection of 0.2 to 1 mg may provide satisfactory pain relief for up to 24 hours. (Caution: this is only 0.4 to 2 mL of the 5 mg/10 mL ampul or 0.2 to 1 mL of the 10 mg/10 mL ampul of DURAMORPH).

- Do not inject intrathecally more than 2 mL of the 5 mg/10 mL ampul or 1 mL of the 10 mg/10 mL ampul.
- Repeated intrathecal injections of DURAMORPH are not recommended. If pain recurs, consider alternative routes of administration
- A constant intravenous infusion of naloxone, 0.6 mg/hr, for 24 hours after intrathecal injection may be used to reduce the incidence of potential side effects.

2.6 Safe Reduction and Discontinuation of DURAMORPH

When a patient who has been treated with a regimen of opioid analgesics including DURAMORPH regularly and may be physically dependent or no longer requires therapy with DURAMORPH, taper the dose gradually while monitoring carefully for signs and symptoms of withdrawal. If the patient develops these signs or symptoms, raise the dose to the previous level and taper more slowly, either by increasing the interval between decreases, decreasing the amount of change in dose, or both. Do not rapidly reduce or abruptly discontinue DURAMORPH in patients who may be physically dependant on opioids. [see Warnings and Precautions (5.16), Drug Abuse and Dependence (9.3)].

3 DOSAGE FORMS AND STRENGTHS

Injection: 5 mg per 10 mL (0.5 mg/mL) Preservative-free amber glass ampuls
Injection: 10 mg per 10 mL (1 mg/mL) Preservative-free amber glass ampuls

4 CONTRAINDICATIONS

DURAMORPH is contraindicated in patients with:

- Significant respiratory depression [see Warnings and Precautions (5.3)]
- Acute or severe bronchial asthma in an unmonitored setting or in the absence of resuscitative equipment [see Warnings and Precautions (5.9)]
- Concurrent use of monoamine oxidase inhibitors (MAOIs) or use of MAOIs within the last 14 days [see Warnings and Precautions (5.10), Drug Interactions (7)]
- Known or suspected gastrointestinal obstruction, including paralytic ileus [see Warnings and Precautions (5.14)]
- Hypersensitivity to morphine (e.g., anaphylaxis) [see Adverse Reactions (6)]

Neuraxial administration of DURAMORPH is contraindicated in patients with:

- Infection at the injection microinfusion site [see Warnings and Precautions (5.1)]
- Concomitant anticoagulant therapy [see Warnings and Precautions (5.1)]
- Uncontrolled bleeding diathesis [see Warnings and Precautions (5.1)]
- The presence of any other concomitant therapy or medical condition which would render epidural or intrathecal administration of medication especially hazardous.

5 WARNINGS AND PRECAUTIONS

5.1 Risks with Neuraxial Administration

Control of pain by neuraxial opioid delivery is always accompanied by considerable risk to the patient and requires a high level of skill to be successfully accomplished. The task of treating these patients must be undertaken by experienced clinical teams, well-versed in patient selection, evolving technology and emerging standards of care.

In the case of epidural or intrathecal administration, DURAMORPH should be administered by or under the direction of a physician experienced in the techniques and familiar with the patient management problems associated with epidural or intrathecal drug administration. The physician should be familiar with patient conditions (such as infection at the injection site, bleeding diathesis, anticoagulant therapy, etc.) which call infection at the injection site, bleeding diathesis, anticoagulant therapy, etc.) which call for special evaluation of the benefit versus risk potential.

Because epidural administration has been associated with less potential for immediate or late adverse effects than intrathecal administration, the epidural route should be used whenever possible.

For safety reasons, it is recommended that administration of DURAMORPH by the epidural or intrathecal routes be limited to the lumbar area. Thoracic epidural administration has been shown to dramatically increase the incidence of early and late respiratory depression even with doses of 1 to 2 mg.

Because of the risk of severe adverse effects when the epidural or intrathecal route of administration is employed, patients must be observed in a fully equipped and staffed environment for at least 24 hours after the initial dose.

The facility must be equipped to resuscitate patients with severe opiate overdosage, and the personnel must be familiar with the use and limitations of specific opioid overdose reversal agents in (naloxone, naltrexone) in such cases.

Parenteral administration of narcotics in patients receiving epidural or intrathecal morphine may result in overdosage.

5.2 Addiction, Abuse, and Misuse

DURAMORPH contains morphine, a Schedule II controlled substance. As an opioid, DURAMORPH exposes users to the risks of addiction, abuse, and misuse [see Drug Abuse and Dependence (9)].

Although the risk of addiction in any individual is unknown, it can occur in patients appropriately prescribed DURAMORPH. Addiction can occur at recommended dosages and if the drug is misused or abused. The risk of opioid-related overdose or overdose-related death is increased with higher opioid doses, and this risk persists over the course of therapy. In postmarketing studies, addiction, abuse, misuse and fatal and non-fatal opioid overdose were observed in patients with long-term opioid use [see Adverse Reactions (6.2)].

Assess each patient’s risk for opioid addiction, abuse, or misuse prior to prescribing DURAMORPH, and monitor all patients receiving DURAMORPH for the development of these behaviors and conditions. Risks are increased in patients with a personal or family history of substance abuse (including drug or alcohol abuse or addiction) or mental illness (e.g., major depression). The potential for these risks should not, however, prevent the proper management of pain in any given patient.

Patients at increased risk may be prescribed opioids such as DURAMORPH but use in such patients necessitates intensive counseling about the risks and proper use of DURAMORPH along with intensive monitoring for signs of addiction, abuse, and misuse.

Opioids are sought for nonmedical use and are subject to diversion from legitimate prescribed use. Consider these risks when prescribing or dispensing DURAMORPH. Strategies to reduce these risks include prescribing the drug in the smallest appropriate quantity.

Contact local state professional licensing board or state-controlled substances authority for information on how to prevent and detect abuse or diversion of this product.

5.3 Life-Threatening Respiratory Depression

Serious, life threatening, or fatal respiratory depression has been reported with the use of opioids, even when used as recommended. Respiratory depression, if not immediately recognized and treated, may lead to respiratory arrest and death. Management of respiratory depression may include close observation, supportive measures, and use of opioid overdose reversal agents (e.g., naloxone, nalmefene), depending on the patient’s clinical status [see Overdosage (10)]. Carbon dioxide (CO) retention from opioid induced respiratory depression can exacerbate the sedating effects of opioids.

While serious, life threatening, or fatal respiratory depression can occur at any time during the use of DURAMORPH, the risk is greatest during the initiation of therapy or following a dosage increase. This respiratory depression and/or respiratory arrest may be severe and could require intervention.

- Because of delay in maximum CNS effect with intravenously administered drug (30 min), rapid administration may result in overdosing.
- Single-dose neuraxial administration may result in acute or delayed respiratory depression for periods at least as long as 24 hours.
- Severe respiratory depression up to 24 hours following epidural or intrathecal administration has been reported.
- Intrathecal use has been associated with a higher incidence of respiratory depression than epidural use.
- Thoracic administration has been shown to dramatically increase the incidence of early and late respiratory depression even at doses of 1 to 2 mg.

Because of the risk of severe adverse effects when the epidural or intrathecal route of administration is employed, patients must be observed in a fully equipped and staffed environment for at least 24 hours after the initial dose. The facility must be equipped to resuscitate patients with severe opiate overdosage, and the personnel must be familiar with the use and limitations of specific narcotic antagonists (naloxone, naltrexone) in such cases.

To reduce the risk of respiratory depression, proper dosing and titration of DURAMORPH are essential [see Dosage and Administration (2)]. Overestimating the DURAMORPH dosage can result in a fatal overdose with the first dose.

Opioids can cause sleep-related breathing disorders including central sleep apnea (CSA) and sleep-related hypoxemia. Opioid use increases the risk of CSA in a dose dependent fashion. In patients who present with CSA, consider decreasing the opioid dosage using best practices for opioid taper [see Dosage and Administration (2.6)]

5.4 Risks from Concomitant Use with Benzodiazepines or Other CNS Depressants

Profound sedation, respiratory depression, coma, and death may result from concomitant use of DURAMORPH with benzodiazepines and/or other CNS depressants, including alcohol (e.g., nonbenzodiazepine sedatives/ hypnotics, anxiolytics, tranquilizers, muscle relaxants, general anesthetics, antipsychotics, gabapentinoids [gabapentin or pregabalin], and other opioids). Because of these risks, reserve concomitant prescribing of these drugs for use in patients for whom alternative treatment options are inadequate.

Use of neuroleptics in conjunction with neuraxial morphine may increase the risk of respiratory depression.

Observational studies have demonstrated that concomitant use of opioid analgesics and benzodiazepines increases the risk of drug related mortality compared to use of opioid analgesics alone. Because of similar pharmacological properties, it is reasonable to expect similar risk with the concomitant use of other CNS depressant drugs with opioid analgesics [see Drug Interactions (7)].

If the decision is made to prescribe a benzodiazepine or other CNS depressant concomitantly with an opioid analgesic, prescribe the lowest effective dosages and minimum durations of concomitant use. In patients already receiving an opioid analgesic, prescribe a lower initial dose of the benzodiazepine or other CNS depressant than indicated in the absence of an opioid, and titrate based on clinical response. If an opioid analgesic is initiated in a patient already taking a benzodiazepine or other CNS depressant, prescribe a lower initial dose of the opioid analgesic, and titrate based on clinical response. Monitor patients closely for signs and symptoms of respiratory depression and sedation.

5.5 Neonatal Opioid Withdrawal Syndrome

Prolonged use of DURAMORPH during pregnancy can result in withdrawal in the neonate. Neonatal opioid withdrawal syndrome, unlike opioid withdrawal syndrome in adults, may be life threatening if not recognized and treated and requires management according to protocols developed by neonatology experts. Observe newborns for signs of neonatal opioid withdrawal syndrome and manage accordingly. Advise pregnant women using opioids for a prolonged period of the risk of neonatal opioid withdrawal syndrome and ensure that management by neonatology experts will be available at delivery [see Use in Specific Populations (8.1)].

5.6 Risk of Tolerance and Myoclonic Activity

Patients sometimes manifest unusual acceleration of neuraxial morphine requirements, which may cause concern regarding systemic absorption and the hazards of large doses; these patients may benefit from hospitalization and detoxification. Two cases of myoclonic-like spasm of the lower extremities have been reported in patients receiving more than 20 mg/day of intrathecal morphine. After detoxification, it might be possible to resume treatment at lower doses, and some patients have been successfully changed from continuous epidural morphine to continuous intrathecal morphine. Repeat detoxification may be indicated at a later date. The upper daily dosage limit for each patient during continuing treatment must be individualized.

5.7 Chest Wall Rigidity

Rapid intravenous administration may result in chest wall rigidity.

5.8 Opioid-Induced Hyperalgesia and Allodynia

Opioid Induced Hyperalgesia (OIH) occurs when an opioid analgesic paradoxically causes an increase in pain, or an increase in sensitivity to pain. This condition differs from tolerance, which is the need for increasing doses of opioids to maintain a defined effect [see Dependence (9.3)]. Symptoms of OIH include (but may not be limited to) increased levels of pain upon opioid dosage increase, decreased levels of pain upon opioid dosage decrease, or pain from ordinarily nonpainful stimuli (allodynia). These symptoms may suggest OIH only if there is no evidence of underlying disease progression, opioid tolerance, opioid withdrawal, or addictive behavior.

Cases of OIH have been reported, both with short-term and longer-term use of opioid analgesics. Though the mechanism of OIH is not fully understood, multiple biochemical pathways have been implicated. Medical literature suggests a strong biologic plausibility between opioid analgesics and OIH and allodynia. If a patient is suspected to be experiencing OIH, carefully consider appropriately decreasing the dose of the current opioid analgesic or opioid rotation (safely switching the patient to a different opioid moiety) [see Dosage and Administration (2.6), Warnings and Precautions (5.16)].

5.9 Life-Threatening Respiratory Depression in Patients with Chronic Pulmonary Disease or in Elderly, Cachectic, or Debilitated Patients

The use of DURAMORPH in patients with acute or severe bronchial asthma in an unmonitored setting or in the absence of resuscitative equipment is contraindicated.

Patients with Chronic Pulmonary Disease: Patients with significant chronic obstructive pulmonary disease or cor pulmonale, and those with a substantially decreased respiratory reserve, hypoxia, hypercapnia, or pre-existing respiratory depression are at increased risk of decreased respiratory drive including apnea, even at recommended doses of DURAMORPH [see Warnings and Precautions (5.3)].

Elderly, Cachectic, or Debilitated Patients: Life-threatening respiratory depression is more likely to occur in elderly, cachectic, or debilitated patients because they may have altered pharmacokinetics or altered clearance compared to younger, healthier patients [see Warnings and Precautions (5.3)].

Monitor such patients closely, particularly when initiating and titrating DURAMORPH and when DURAMORPH is given concomitantly with other drugs that depress respiration [see Warnings and Precautions (5.3, 5.4), Drug Interactions (7)]. Alternatively, consider the use of non-opioid analgesics in these patients.

5.10 Interaction with Monoamine Oxidase Inhibitors

Monoamine oxidase inhibitors (MAOIs) may potentiate the effects of morphine, including respiratory depression, coma, and confusion. DURAMORPH should not be used in patients taking MAOIs or within 14 days of stopping such treatment [see Drug Interactions (7)].

5.11 Adrenal Insufficiency

Cases of adrenal insufficiency have been reported with opioid use, more often following greater than one month of use. Presentation of adrenal insufficiency may include nonspecific symptoms and signs including nausea, vomiting, anorexia, fatigue, weakness, dizziness, and low blood pressure. If adrenal insufficiency is suspected, confirm the diagnosis with diagnostic testing as soon as possible. If adrenal insufficiency is diagnosed, treat with physiologic replacement doses of corticosteroids. Wean the patient off of the opioid to allow adrenal function to recover and continue corticosteroid treatment until adrenal function recovers. Other opioids may be tried as some cases reported use of a different opioid without recurrence of adrenal insufficiency. The information available does not identify any particular opioids as being more likely to be associated with adrenal insufficiency.

5.12 Severe Hypotension

DURAMORPH may cause severe hypotension including orthostatic hypotension and syncope in ambulatory patients. There is increased risk in patients whose ability to maintain blood pressure has already been compromised by a reduced blood volume or concurrent administration of certain CNS depressant drugs (e.g., phenothiazines or general anesthetics) [see Drug Interactions (7)]. Monitor these patients for signs of hypotension after initiating or titrating the dosage of DURAMORPH. In patients with circulatory shock, DURAMORPH may cause vasodilation that can further reduce cardiac output and blood pressure. Avoid the use of DURAMORPH in patients with circulatory shock.

5.13 Risks of Use in Patients with Increased Intracranial Pressure, Brain Tumors, Head Injury, or Impaired Consciousness

In patients who may be susceptible to the intracranial effects of CO2 retention (e.g., those with evidence of increased intracranial pressure or brain tumors), DURAMORPH may reduce respiratory drive, and the resultant CO2 retention can further increase intracranial pressure. Monitor such patients for signs of sedation and respiratory depression, particularly when initiating therapy with DURAMORPH. DURAMORPH should be used with extreme caution in patients with head injury or increased intracranial pressure. Pupillary changes (miosis) from morphine may obscure the existence, extent and course of intracranial pathology. High doses of neuraxial morphine may produce myoclonic events [see Warnings and Precautions (5.6)]. Clinicians should maintain a high index of suspicion for adverse drug reactions when evaluating altered mental status or movement abnormalities in patients receiving this modality of treatment.

Opioids may also obscure the clinical course in a patient with a head injury. Avoid the use of DURAMORPH in patients with impaired consciousness or coma.

5.14 Risks of Gastrointestinal Complications

DURAMORPH is contraindicated in patients with known or suspected gastrointestinal obstruction, including paralytic ileus.

The morphine in DURAMORPH may cause spasm of the sphincter of Oddi. Opioids may cause increases in serum amylase. Monitor patients with biliary tract disease, including acute pancreatitis for worsening symptoms. As significant morphine is released into the systemic circulation from neuraxial administration, the ensuing smooth muscle hypertonicity may result in biliary colic.

Cases of opioid-induced esophageal dysfunction (OIED) have been reported in patients taking opioids. The risk of OIED may increase as the dose and/or duration of opioids increases. Regularly evaluate patients for signs and symptoms of OIED (e.g., dysphagia, regurgitation, non-cardiac chest pain) and, if necessary, adjust opioid therapy as clinically appropriate [see Clinical Pharmacology (12.2)].

5.15 Risk of Seizures

The morphine in DURAMORPH may increase the frequency of seizures in patients with seizure disorders, and may increase the risk of seizures occurring in other clinical setting associated with seizures. Monitor patients with a history of seizure disorders for worsened seizure control during DURAMORPH therapy.

Excitation of the central nervous system, resulting in convulsions, may accompany high doses of morphine given intravenously.

5.16 Withdrawal

Avoid the use of mixed agonist/antagonist (e.g., pentazocine, nalbuphine, and butorphanol) or partial agonist (e.g., buprenorphine) analgesics in patients who are receiving a full opioid agonist analgesic, including DURAMORPH. In these patients, mixed agonist/antagonist and partial agonist analgesics may reduce the analgesic effect and/or precipitate withdrawal symptoms [see Drug Interactions (7)].

When discontinuing DURAMORPH, gradually taper the dosage [see Dosage and Administration (2.6)]. Do not rapidly reduce or abruptly discontinue DURAMORPH [see Drug Abuse and Dependence (9.3)].

5.17 Risks of Use in Patients with Urinary System Disorders

Urinary retention, which may persist 10 to 20 hours following single epidural or intrathecal administration, is frequently associated with neuraxial opioid administration and must be anticipated, more frequently in male patients than female patients. Urinary retention may also occur during the first several days of hospitalization for the initiation of continuous intrathecal or epidural morphine therapy. Early recognition of difficulty in urination and prompt intervention in cases of urinary retention is indicated. Patients who develop urinary retention have responded to cholinomimetic treatment and/or judicious use of catheters.

5.18 Risks of Use in Ambulatory Patients

Patients with reduced circulating blood volume, impaired myocardial function or on sympatholytic drugs should be monitored for the possible occurrence of orthostatic hypotension, a frequent complication in single-dose neuraxial morphine analgesia.

6 ADVERSE REACTIONS

The following serious adverse reactions are described, or described in greater detail, in other sections:

- Addiction, Abuse, and Misuse [see Warnings and Precautions (5.2)]
- Life-Threatening Respiratory Depression [see Warnings and Precautions (5.3)]
- Interactions with Benzodiazepines or Other CNS Depressants [see Warnings and Precautions (5.4)]
- Neonatal Opioid Withdrawal Syndrome [see Warnings and Precautions (5.5)]
- Myoclonic Activity [see Warnings and Precautions (5.6)]
- Opioid-Induced Hyperalgesia and Allodynia [see Warnings and Precautions (5.8)]
- Adrenal Insufficiency [see Warnings and Precautions (5.11)]
- Severe Hypotension [see Warnings and Precautions (5.12)]
- Gastrointestinal Adverse Reactions [see Warnings and Precautions (5.14)]
- Seizures[see Warnings and Precautions (5.15)]
- Withdrawal[see Warnings and Precautions (5.16)]
- Urinary Retention [seeWarnings and Precautions (5.17)]
- Orthostatic Hypotension [see Warnings and Precautions (5.18)]

The following adverse reactions associated with the use of morphine were identified in clinical studies or postmarketing reports. Because some of these reactions were reported voluntarily from a population of uncertain size, it is not always possible to reliably estimate their frequency or establish a causal relationship to drug exposure.

The most serious adverse reactions encountered during administration of DURAMORPH were respiratory depression and/or respiratory arrest.

Cardiovascular System: While low doses of intravenously administered morphine have little effect on cardiovascular stability, high doses are excitatory, resulting from sympathetic hyperactivity and increase in circulating catecholamines.

Central Nervous System: myoclonus, seizures, dysphoric reactions, toxic psychosis, dizziness, euphoria, anxiety, confusion, headache. Lumbar puncture-type headache is encountered in a significant minority of cases for several days following intrathecal catheter implantation and generally responds to bed rest and/or other conventional therapy.

Gastrointestinal System: Nausea, vomiting, constipation

Skin: Generalized pruritus, urticaria, wheals, and/or local tissue irritation. Single-dose epidural or intrathecal administration is accompanied by a high incidence of dose-related generalized pruritus.

Urinary System: Urinary retention, oliguria.

Peripheral edema: There are several reports of peripheral edema

Other: Other adverse reactions reported following morphine therapy include depression of cough reflex, interference with thermal regulation, peripheral edema.

Serotonin syndrome: Cases of serotonin syndrome, a potentially life-threatening condition, have been reported during concomitant use of opioids with serotonergic drugs.

Adrenal insufficiency: Cases of adrenal insufficiency have been reported with opioid use, more often following greater than one month of use.

Anaphylaxis: Anaphylaxis has been reported with ingredients contained in DURAMORPH.

Androgen deficiency: Cases of androgen deficiency have occurred with use of opioids for an extended period of time. [see Clinical Pharmacology (12.2)].

Hyperalgesia and Allodynia: Cases of hyperalgesia and allodynia have been reported with opioid therapy of any duration [see Warnings and Precautions (5.8)].

Hypoglycemia: Cases of hypoglycemia have been reported in patients taking opioids. Most reports were in patients with at least one predisposing risk factor (e.g., diabetes).

Opioid-induced esophageal dysfunction (OIED): Cases of OIED have been reported in patients taking opioids and may occur more frequently in patients taking higher doses of opioids, and/or in patients taking opioids longer term [see Warnings and Precautions (5.14)].

Adverse Reactions from Observational Studies

A prospective, observational cohort study estimated the risks of addiction, abuse, and misuse in patients initiating long-term use of Schedule II opioid analgesics between 2017 and 2021. Study participants included in one or more analyses had been enrolled in selected insurance plans or health systems for at least one year, were free of at least one outcome at baseline, completed a minimum number of follow-up assessments, and either: 1) filled multiple extended-release/long-acting opioid analgesic prescriptions during a 90-day period (n=978); or 2) filled any Schedule II opioid analgesic prescriptions covering at least 70 of 90 days (n=1,244). Those included also had no dispensing of the qualifying opioids in the previous 6 months.

Over 12 months:

- approximately 1% to 6% of participants across the two cohorts newly met criteria for addiction, as assessed with two validated interview-based measures of moderate-to-severe opioid use disorderbasedonDiagnosticandStatisticalManualofMentalDisorders,FifthEdition(DSM-5) criteria, and
- approximately9%and22%ofparticipantsacrossthetwocohortsnewlymetcriteriafor prescription opioid abuse and misuse [defined in Drug Abuse and Dependence (9.2)], respectively, as measured with a validated self-reported instrument.

A retrospective, observational cohort study estimated the risk of opioidinvolved overdose or opioid overdose-related death in patients with new long-term use of Schedule II opioid analgesics from 2006 through 2016 (n=220,249). Included patients had been enrolled in either one of two commercial insurance programs, one managed care program, or one Medicaid program for at least 9 months. New long-term use was defined as having Schedule II opioid analgesic prescriptions covering at least 70 days’ supply over the 3 months prior to study entry and none during the preceding 6 months. Patients were excluded if they had an opioid-involved overdose in the 9 months prior to study entry. Overdose was measured using a validated medical code-based algorithm with linkage to the National Death Index database. The 5-year cumulative incidence estimates for opioid-involved overdose or opioid overdose-related death ranged from approximately 1.5% to 4% across study sites, counting only the first event during follow-up. Approximately 17% of first opioid overdoses observed over the entire study period (5-11 years, depending on the study site) were fatal. Higher baseline opioid dose was the strongest and most consistent predictor of opioid-involved overdose or opioid overdose-related death. Study exclusion criteria may have selected patients at lower risk of overdose, and substantial loss to follow-up (approximately 80%) also may have biased estimates.

The risk estimates from the studies described above may not be generalizable to all patients receiving opioid analgesics, such as those with exposures shorter or longer than the duration evaluated in the studies.

7 DRUG INTERACTIONS

Table 1 includes clinically significant drug interactions with DURAMORPH.

Table 1 Clinically Significant Drug Interactions with DURAMORPH

Benzodiazepines and Other Central Nervous System (CNS) Depressants
Clinical Impact: | Due to additive pharmacologic effect, the concomitant use of benzodiazepines or other CNS depressants, including alcohol, can increase the risk of hypotension, respiratory depression, profound sedation, coma, and death. The depressant effects of morphine are potentiated by the presence of other CNS depressants. Use of neuroleptics in conjunction with neuraxial morphine may increase the risk of respiratory depression [see Warnings and Precautions (5.4)].
Intervention: | Reserve concomitant prescribing of these drugs for use in patients for whom alternative treatment options are inadequate. Limit dosages and durations to the minimum required. Monitor closely for signs of respiratory depression and sedation [see Warnings and Precautions (5.4)].
Examples: | Benzodiazepines and other sedatives/hypnotics, anxiolytics, tranquilizers, muscle relaxants, general anesthetics, antipsychotics, psychotropic drugs, antihistamines, neuroleptics, gabapentinoids (gabapentin or pregabalin), other opioids, alcohol.
Serotonergic Drugs
Clinical Impact: | The concomitant use of opioids with other drugs that affect the serotonergic neurotransmitter system has resulted in serotonin syndrome.
Intervention: | If concomitant use is warranted, carefully observe the patient, particularly during treatment initiation and dose adjustment. Discontinue DURAMORPH if serotonin syndrome is suspected.
Examples: | Selective serotonin reuptake inhibitors (SSRIs), serotonin and norepinephrine reuptake inhibitors (SNRIs), tricyclic antidepressants (TCAs), triptans, 5-HT3 receptor antagonists, drugs that effect the serotonin neurotransmitter system (e.g., mirtazapine, trazodone, tramadol), certain muscle relaxants (i.e., cyclobenzaprine, metaxalone), monoamine oxidase inhibitors (those intended to treat psychiatric disorders and also others, such as linezolid and intravenous methylene blue).
Monoamine Oxidase Inhibitors (MAOIs)
Clinical Impact: | MAOI interactions with opioids may manifest as serotonin syndrome or opioid toxicity (e.g., respiratory depression, coma) [see Warnings and Precautions (5.10)].
 | Do not use DURAMORPH in patients taking MAOIs or within 14 days of stopping such treatment.
Intervention: | If urgent use of an opioid is necessary, use test doses and frequent titration of small doses of other opioids (such as oxycodone, hydromorphone, oxymorphone, hydrocodone, or buprenorphine) to treat pain while closely monitoring blood pressure and signs and symptoms of CNS and respiratory depression.
Examples: | phenelzine, tranylcypromine, linezolid
Mixed Agonist/Antagonist and Partial Agonist Opioid Analgesics
Clinical Impact: | Clinical Impact: May reduce the analgesic effect of DURAMORPH and/or precipitate withdrawal symptoms.
Intervention: | Avoid concomitant use.
Examples: | Butorphanol, nalbuphine, pentazocine, buprenorphine.
Muscle Relaxants
Clinical Impact: | Morphine may enhance the neuromuscular blocking action of skeletal muscle relaxants and produce an increased degree of respiratory depression.
Intervention: | Monitor patients for signs of respiratory depression that may be greater than otherwise expected and decrease the dosage of DURAMORPH and/or the muscle relaxant as necessary.
Diuretics
Clinical Impact: | Opioids can reduce the efficacy of diuretics by inducing the release of antidiuretic hormone.
Intervention: | Monitor patients for signs of diminished diuresis and/or effects on blood pressure and increase the dosage of the diuretic as needed.
Anticholinergic Drugs
Clinical Impact: | The concomitant use of anticholinergic drugs may increase risk of urinary retention and/or severe constipation, which may lead to paralyticileus.
Intervention: | Monitor patients for signs of urinary retention or reduced gastric motility when DURAMORPH is used concomitantly with anticholinergic drugs.
Oral P2Y12 Inhibitors
Clinical Impact: | The co-administration of oral P2Y12 inhibitors and intravenous morphine sulfate can decrease the absorption and peak concentration of oral P2Y12 inhibitors and delay the onset of the antiplatelet effect.
Intervention: | Consider the use of a parenteral antiplatelet agent in the setting of acute coronary syndrome requiring co-administration of intravenous morphine sulfate.
Examples: | clopidogrel, prasugrel, ticagrelor

8 USE IN SPECIFIC POPULATIONS

8.1 Pregnancy

Risk Summary

Use of opioid analgesics for an extended period of time during pregnancy may cause neonatal opioid withdrawal syndrome [see Warnings and Precautions (5.5)]. Available data with DURAMORPH in pregnant women are insufficient to inform a drug-associated risk for major birth defects and miscarriage. There are adverse outcomes reported with fetal exposure to opioid analgesics (see Clinical Considerations). Published studies with morphine use during pregnancy have not reported a clear association with morphine and major birth defects [see Human Data]. In published animal reproduction studies, morphine administered subcutaneously during the early gestational period produced neural tube defects (i.e., exencephaly and cranioschisis) at 5 and 16 times the human daily dose of 60 mg based on body surface area (HDD) in hamsters and mice, respectively, lower fetal body weight and increased incidence of abortion at 0.4 times the HDD in the rabbit, growth retardation at 6 times the HDD in the rat, and axial skeletal fusion and cryptorchidism at 16 times the HDD in the mouse. Administration of morphine sulfate to pregnant rats during organogenesis and through lactation resulted in cyanosis, hypothermia, decreased brain weights, pup mortality, decreased pup body weights, and adverse effects on reproductive tissues at 3-4 times the HDD; and long-term neurochemical changes in the brain of offspring which correlate with altered behavioral responses that persist through adulthood at exposures comparable to and less than the HDD [see Animal Data]. Based on animal data, advise pregnant women of the potential risk to a fetus.

The background risk of major birth defects and miscarriage for the indicated population is unknown. All pregnancies have a background risk of birth defect, loss, or other adverse outcomes. In the U.S. general population, the estimated background risk of major birth defects and miscarriage in clinically recognized pregnancies is 2 to 4% and 15 to 20%, respectively.

Clinical Considerations

Fetal/Neonatal Adverse Reactions

Use of opioid analgesics for an extended period of time during pregnancy for medical or nonmedical purposes can result in physical dependence in the neonate and neonatal opioid withdrawal syndrome shortly after birth. Neonatal opioid withdrawal syndrome presents as irritability, hyperactivity and abnormal sleep pattern, high pitched cry, tremor, vomiting, diarrhea, and failure to gain weight. The onset, duration, and severity of neonatal opioid withdrawal syndrome vary based on the specific opioid used, duration of use, timing and amount of last maternal use, and rate of elimination of the drug by the newborn. Observe newborns for symptoms of neonatal opioid withdrawal syndrome and manage accordingly [see Warnings and Precautions (5.5)].

Labor or Delivery

Opioids cross the placenta and may produce respiratory depression and psychophysiologic effects in neonates. An opioid overdose reversal agent, such as naloxone or nalmefene, must be available for reversal of opioid induced respiratory depression in the neonate. DURAMORPH is not recommended for use in women during and immediately prior to labor, when use of shorter-acting analgesics or other analgesic techniques are more appropriate. Opioid analgesics, including DURAMORPH, can prolong labor through actions that temporarily reduce the strength, duration, and frequency of uterine contractions. However, this effect is not consistent and may be offset by an increased rate of cervical dilatation, which tends to shorten labor. Monitor neonates exposed to opioid analgesics during labor for signs of excess sedation and respiratory depression.

Data

Human Data

The results from a population-based prospective cohort, including 70 women exposed to morphine during the first trimester of pregnancy and 448 women exposed to morphine at any time during pregnancy, indicate no increased risk for congenital malformations. However, these studies cannot definitely establish the absence of any risk because of methodological limitations, including small sample size and nonrandomized study design.

Animal Data

Formal reproductive and developmental toxicology studies for morphine have not been conducted. Exposure margins for the following published study reports are based on human daily dose of 60 mg morphine using a body surface area comparison (HDD).

Neural tube defects (exencephaly and cranioschisis) were noted following subcutaneous administration of morphine sulfate (35-322 mg/kg) on Gestation Day 8 to pregnant hamsters (4.7 to 43.5 times the HDD). A no adverse effect level was not defined in this study and the findings cannot be clearly attributed to maternal toxicity. Neural tube defects (exencephaly), axial skeletal fusions, and cryptorchidism were reported following a single subcutaneous (SC) injection of morphine sulfate to pregnant mice (100-500 mg/kg) on Gestation Day 8 or 9 at 200 mg/kg or greater (16 times the HDD) and fetal resorption at 400 mg/kg or higher (32 times the HDD). No adverse effects were noted following 100 mg/kg morphine in this model (8 times the HDD). In one study, following continuous subcutaneous infusion of doses greater than or equal to 2.72 mg/kg to mice (0.2 times the HDD), exencephaly, hydronephrosis, intestinal hemorrhage, split supraoccipital, malformed sternebrae, and malformed xiphoid were noted. The effects were reduced with increasing daily dose; possibly due to rapid induction of tolerance under these infusion conditions. The clinical significance of this report is not clear.

Decreased fetal weights were observed in pregnant rats treated with 20 mg/kg/day morphine sulfate (3.2 times the HDD) from Gestation Day 7 to 9. There was no evidence of malformations despite maternal toxicity (10% mortality). In a second rat study, decreased fetal weight and increased incidences of growth retardation were noted at 35 mg/kg/day (5.7 times the HDD) and there was a reduced number of fetuses at 70 mg/kg/day (11.4 times the HDD) when pregnant rats were treated with 10, 35, or 70 mg/kg/day morphine sulfate via continuous infusion from Gestation Day 5 to 20. There was no evidence of fetal malformations or maternal toxicity.

An increased incidence of abortion was noted in a study in which pregnant rabbits were treated with 2.5 (0.8 times the HDD) to 10 mg/kg morphine sulfate via subcutaneous injection from Gestation Day 6 to 10. In a second study, decreased fetal body weights were reported following treatment of pregnant rabbits with increasing doses of morphine (10-50 mg/kg/day) during the pre-mating period and 50 mg/kg/day (16 times the HDD) throughout the gestation period. No overt malformations were reported in either publication; although only limited endpoints were evaluated.

In published studies in rats, exposure to morphine during gestation and/or lactation periods is associated with: decreased pup viability at 12.5 mg/kg/day or greater (2 times the HDD); decreased pup body weights at 15 mg/kg/day or greater (2.4 times the HDD); decreased litter size, decreased absolute brain and cerebellar weights, cyanosis, and hypothermia at 20 mg/kg/day (3.2 times the HDD); alteration of behavioral responses (play, social-interaction) at 1 mg/kg/day or greater (0.2 times the HDD); alteration of maternal behaviors (e.g., decreased nursing and pup retrievals) in mice at 1 mg/kg or higher (0.08 times the HDD) and rats at 1.5 mg/kg/day or higher (0.2 times the HDD); and a host of behavioral abnormalities in the offspring of rats, including altered responsiveness to opioids at 4 mg/kg/day (0.7 times the HDD) or greater.

Fetal and/or postnatal exposure to morphine in mice and rats has been shown to result in morphological changes in fetal and neonatal brain and neuronal cell loss, alteration of a number of neurotransmitter and neuromodulator systems, including opioid and nonopioid systems, and impairment in various learning and memory tests that appear to persist into adulthood. These studies were conducted with morphine treatment usually in the range of 4 to 20 mg/kg/day (0.7 to 3.2 times the HDD).

Additionally, delayed sexual maturation and decreased sexual behaviors in female offspring at 20 mg/kg/day (3.2 times the HDD), and decreased plasma and testicular levels of luteinizing hormone and testosterone, decreased testes weights, seminiferous tubule shrinkage, germinal cell aplasia, and decreased spermatogenesis in male offspring were also observed at 20 mg/kg/day (3.2 times the HDD). Decreased litter size and viability were observed in the offspring of male rats that were intraperitoneally administered morphine sulfate for 1 day prior to mating at 25 mg/kg/day (4.1 times the HDD) and mated to untreated females. Decreased viability and body weight and/or movement deficits in both first and second generation offspring were reported when male mice were treated for 5 days with escalating doses of 120 to 240 mg/kg/day morphine sulfate (9.7 to 19.5 times the HDD) or when female mice treated with escalating doses of 60 to 240 mg/kg/day (4.9 to 19.5 times the HDD) followed by a 5- day treatment-free recovery period prior to mating. Similar multigenerational findings were also seen in female rats pre-gestationally treated with escalating doses of 10 to 22 mg/kg/day morphine (1.6 to 3.6 times the HDD).

8.2 Lactation

Risk Summary

Morphine is present in breast milk. Published lactation studies report variable concentrations of morphine in breast milk with administration of immediate-release morphine to nursing mothers in the early postpartum period with a milk-to-plasma morphine AUC ratio of 2.5:1 measured in one lactation study. However, there is insufficient information to determine the effects of morphine on the breastfed infant and the effects of morphine on milk production. Lactation studies have not been conducted with DURAMORPH, and no information is available on the effects of the drug on the breastfed infant or the effects of the drug on milk production.

The developmental and health benefits of breastfeeding should be considered along with the mother’s clinical need for DURAMORPH and any potential adverse effects on the breastfed infant from DURAMORPH or from the underlying maternal condition.

Clinical Considerations

Monitor infants exposed to DURAMORPH through breast milk for excess sedation and respiratory depression. Withdrawal symptoms can occur in breastfed infants when maternal administration of morphine is stopped, or when breastfeeding is stopped.

8.3 Females and Males of Reproductive Potential

Infertility

Use of opioids for an extended period of time may cause reduced fertility in females and males of reproductive potential. It is not known whether these effects on fertility are reversible [see Adverse Reactions (6), Clinical Pharmacology (12.2)].

In published animal studies, morphine administration adversely effected fertility and reproductive endpoints in male rats and prolonged estrus cycle in female rats [see Nonclinical Toxicology (13)].

8.4 Pediatric Use

Adequate studies to establish the safety and effectiveness of spinal morphine in pediatric patients have not been performed, and usage in this population is not recommended.

8.5 Geriatric Use

Elderly patients (aged 65 years or older) may have increased sensitivity to DURAMORPH. In general, use caution when selecting a dosage for an elderly patient, usually starting at the low end of the dosing range, reflecting the greater frequency of decreased hepatic, renal, or cardiac function and of concomitant disease or other drug therapy.

Respiratory depression is the chief risk for elderly patients treated with opioids, and has occurred after large initial doses were administered to patients who were not opioid tolerant or when opioids were co-administered with other agents that depress respiration. Titrate the dosage of DURAMORPH slowly in geriatric patients and monitor closely for signs of central nervous system and respiratory depression [see Warnings and Precautions (5.9)].

The pharmacodynamic effects of neuraxial morphine in the elderly are more variable than in the younger population. Patients will vary widely in the effective initial dose, rate of development of tolerance and the frequency and magnitude of associated adverse effects as the dose is increased. Initial doses should be based on careful clinical observation following “test doses”, after making due allowances for the effects of the patient’s age and infirmity on his/her ability to clear the drug, particularly in patients receiving epidural morphine.

Morphine is known to be substantially excreted by the kidney, and the risk of adverse reactions to this drug may be greater in patients with impaired renal function. Because elderly patients are more likely to have decreased renal function, care should be taken in dose selection, and it may be useful to monitor renal function.

8.6 Hepatic or Renal Impairment

The elimination half-life of morphine may be prolonged in patients with reduced metabolic rates and with hepatic and/or renal dysfunction. Hence, care should be exercised in administering DURAMORPH epidurally to patients with these conditions. High blood morphine levels, due to reduced clearance, may take several days to develop.

9 DRUG ABUSE AND DEPENDENCE

9.1 Controlled Substance

DURAMORPH contains morphine, a Schedule II controlled drug substance.

9.2 Abuse

DURAMORPH contains morphine, a substance with high potential for misuse and abuse, which can lead to the development of substance use disorder, including addiction [see Warnings and Precautions (5.2)].

Misuse is the intentional use, for therapeutic purposes, of a drug by an individual in a way other than prescribed by a healthcare provider or for whom it was not prescribed.

Abuse is the intentional, nontherapeutic use of a drug, even once, for its desirable psychological or physiological effects.

Drug addiction is a cluster of behavioral, cognitive, and physiological phenomena that may include a strong desire to take the drug, difficulties in controlling drug use (e.g., continuing drug use despite harmful consequences, giving a higher priority to drug use than other activities and obligations), and possible tolerance or physical dependence.

Misuse and abuse of DURAMORPH increases risk of overdose, which may lead to central nervous system and respiratory depression, hypotension, seizures, and death. The risk is increased with concurrent abuse of DURAMORPH with alcohol and/or other CNS depressants. Abuse of and addiction to opioids in some individuals may not be accompanied by concurrent tolerance and symptoms of physical dependence. In addition, abuse of opioids can occur in the absence of addiction.

All patients treated with opioids require careful and frequent reevaluation for signs of misuse, abuse, and addiction, because use of opioid analgesic products carries the risk of addiction even under appropriate medical use. Patients at high risk of DURAMORPH abuse include those with a history of prolonged use of any opioid, including products containing morphine, those with a history of drug or alcohol abuse, or those who use DURAMORPH in combination with other abused drugs.

“Drug-seeking” behavior is very common in persons with substance use disorders. Drug seeking tactics include emergency calls or visits near the end of office hours, refusal to undergo appropriate examination, testing, or referral, repeated “loss” of prescriptions, tampering with prescriptions, and reluctance to provide prior medical records or contact information for other treating healthcare provider(s). “Doctor shopping” (visiting multiple prescribers to obtain additional prescriptions) is common among people who abuse drugs and people with substance use disorder. Preoccupation with achieving adequate pain relief can be appropriate behavior in a patient with inadequate pain control.

DURAMORPH, like other opioids, can be diverted for nonmedical use into illicit channels of distribution. Careful recordkeeping of prescribing information, including quantity, frequency, and renewal requests, as required by state and federal law, is strongly advised.

Proper assessment of the patient, proper prescribing practices, periodic reevaluation of therapy, and proper dispensing and storage are appropriate measures that help to limit abuse of opioid drugs.

Risks Specific to Abuse of DURAMORPH

Abuse of DURAMORPH poses a risk of overdose and death. The risk is increased with concurrent use of DURAMORPH with alcohol and/or other CNS depressants.

Parenteral drug abuse is commonly associated with transmission of infectious diseases such as hepatitis and HIV.

9.3 Dependence

Both tolerance and physical dependence can develop during use of opioid therapy.

Tolerance is a physiological state characterized by a reduced response to a drug after repeated administration (i.e., a higher dose of a drug is required to produce the same effect that was once obtained at a lower dose).

Physical dependence is a state that develops as a result of a physiological adaptation in response to repeated drug use, manifested by withdrawal signs and symptoms after abrupt discontinuation or a significant dose reduction of a drug.

Withdrawal may be precipitated through the administration of drugs with opioid antagonist activity (e.g., naloxone, nalmefene), mixed agonist/antagonist analgesics (e.g., pentazocine, butorphanol, nalbuphine), or partial agonists (e.g., buprenorphine). Physical dependence may not occur to a clinically significant degree until after several days to weeks of continued use.

DURAMORPH should not be rapidly reduced or abruptly discontinued in a physically dependent patient [see Dosage and Administration (2.6)]. If DURAMORPH is rapidly reduced or abruptly discontinued in a physically dependent patient, a withdrawal syndrome may occur, typically characterized by restlessness, lacrimation, rhinorrhea, perspiration, chills, myalgia, and mydriasis. Other signs and symptoms also may develop, including irritability, anxiety, backache, joint pain, weakness, abdominal cramps, insomnia, nausea, anorexia, vomiting, diarrhea, or increased blood pressure, respiratory rate, or heart rate.

Infants born to mothers physically dependent on opioids will also be physically dependent and may exhibit respiratory difficulties and withdrawal signs [see Use in Specific Populations (8.1)].

10 OVERDOSAGE

Clinical Presentation

Acute overdose with morphine can be manifested by respiratory depression, somnolence progressing to stupor or coma, skeletal muscle flaccidity, cold and clammy skin, constricted pupils, and, in some cases, pulmonary edema, bradycardia, hypotension, hypoglycemia, partial or complete airway obstruction, atypical snoring, and death. Marked mydriasis rather than miosis may be seen with hypoxia in overdose situations [see Clinical Pharmacology (12.2)]. Toxic leukoencephalopathy has been reported after opioid overdose and can present hours, days, or weeks after apparent recovery from the initial intoxication.

Treatment of Overdose

In case of overdose, priorities are the reestablishment of a patent and protected airway and institution of assisted or controlled ventilation, if needed. Employ other supportive measures (including oxygen and vasopressors) in the management of circulatory shock and pulmonary edema as indicated. Cardiac arrest or arrhythmias will require advanced life-support measures.

For clinically significant respiratory or circulatory depression secondary to morphine overdose, administer an opioid overdose reversal agent such as naloxone or nalmefene.

As the duration of effect of naloxone is considerably shorter than that of epidural or intrathecal morphine, repeated administration may be necessary. Patients should be closely observed for evidence of renarcotization.

Because the duration of opioid reversal is expected to be less than the duration of action of morphine in DURAMORPH, particularly with epidural or intrathecal morphine, carefully monitor the patient until spontaneous respiration is reliably reestablished. If the response to an opioid overdose reversal agent is suboptimal or only brief in nature, administer additional reversal agent as directed by the product’s prescribing information.

In an individual physically dependent on opioids, administration of the recommended usual dosage of the opioid overdose reversal agent will precipitate an acute withdrawal syndrome. The severity of the withdrawal symptoms experienced will depend on the degree of physical dependence and the dose of the reversal agent administered. If a decision is made to treat serious respiratory depression in the physically-dependent patient, administration of the reversal agent should be initiated with care and by titration with smaller than usual doses of the reversal agent.

11 DESCRIPTION

DURAMORPH (morphine sulfate injection) is an opioid agonist, available as a sterile, nonpyrogenic isobaric solution of morphine sulfate in strengths of 0.5 mg or 1 mg morphine sulfate per mL, free of antioxidants, preservatives or other potentially neurotoxic additives, and is intended for intravenous, epidural, or intrathecal administration. Morphine is the most important alkaloid of opium and is a phenanthrene derivative. It is available as the sulfate salt, chemically identified as 7,8-Didehydro-4,5-epoxy-17-methyl-(5α,6α)-morphinan-3,6-diol sulfate (2:1) (salt), pentahydrate, with the following structural formula:

(C17H19NO3)2 • H2SO4 • 5H2O Molecular Weight is 758.83

Morphine sulfate USP is an odorless, white crystalline powder with a bitter taste. It has a solubility of 1 in 21 parts of water and 1 in 1000 parts of alcohol, but is practically insoluble in chloroform or ether.
The octanol:water partition coefficient of morphine is 1.42 at physiologic pH and the pKa is 7.9 for the tertiary nitrogen (the majority is ionized at pH 7.4).

Each mL of DURAMORPH contains morphine sulfate, USP 0.5 mg (5 mg/10 mL) or 1 mg (10 mg/10 mL) and sodium chloride 9 mg in Water for Injection. The pH range is 2.5 – 6.5. Contains no preservative. Each 10 mL ampul of DURAMORPH is intended for SINGLE USE ONLY.

12 CLINICAL PHARMACOLOGY

12.1 Mechanism of Action

Morphine is a full opioid agonist and is relatively selective for the mu-opioid receptor, although it can bind to other opioid receptors at higher doses. The principal therapeutic action of morphine is analgesia. Like all full opioid agonists, there is no ceiling effect for analgesia with morphine. Clinically, dosage is titrated to provide adequate analgesia and may be limited by adverse reactions, including respiratory and CNS depression.

The precise mechanism of the analgesic action is unknown. However, specific CNS opioid receptors for endogenous compounds with opioid-like activity have been identified throughout the brain and spinal cord and are thought to play a role in the analgesic effects of this drug.

12.2 Pharmacodynamics

Effects on the Central Nervous System

Morphine produces respiratory depression by direct action on brain stem respiratory centers. The respiratory depression involves a reduction in the responsiveness of the brain stem respiratory centers to both increases in carbon dioxide tension and electrical stimulation.

Morphine causes miosis, even in total darkness. Pinpoint pupils are a sign of opioid overdose but are not pathognomic (e.g., pontine lesions of hemorrhagic or ischemic origins may produce similar findings). Marked mydriasis rather than miosis may be seen due to hypoxia in overdose situations.

Both early and late respiratory depression (up to 24 hours post dosing) have been reported following neuraxial administration. Circulation of the spinal fluid may also result in high concentrations of morphine reaching the brain stem directly.

Effects on the Gastrointestinal Tract and Other Smooth Muscle

Morphine causes a reduction in motility associated with an increase in smooth muscle tone in the antrum of the stomach and duodenum. Digestion of food in the small intestine is delayed and propulsive contractions are decreased. Propulsive peristaltic waves in the colon are decreased, while tone may be increased to the point of spasm, resulting in constipation. Other opioid-induced effects may include a reduction in biliary and pancreatic secretions, spasm of sphincter of Oddi, transient elevations in serum amylase, and opioid-induced esophageal dysfunction (OIED)

Effects on the Cardiovascular System

Morphine produces peripheral vasodilation, which may result in orthostatic hypotension or syncope. Manifestations of histamine release and/or peripheral vasodilation may include pruritis, flushing, red eyes, sweating, and/or orthostatic hypotension.

Effects on the Endocrine System

Opioids inhibit the secretion of adrenocorticotropic hormone (ACTH), cortisol, and lutenizing hormone (LH) in humans [see Adverse Reactions (6)]. They also stimulate prolactin, growth hormone (GH) secretion, and pancreatic secretion of insulin and glucagon.

Use of opioids for an extended period of time may influence the hypothalamic-pituitary-gonadal-axis, leading to androgen deficiency that may manifest as low libido, impotence, erectile dysfunction, amenorrhea, or infertility. The causal role of opioids in the clinical syndrome of hypogonadism is unknown because the various medical, physical, lifestyle, and psychological stressors that may influence gonadal hormone levels have not been adequately controlled for in studies conducted to date [see Adverse Reactions (6)].

Effects on the Immune System

Opioids have been shown to have a variety of effects on components of the immune system in in vitro and animal models. The clinical significance of these findings is unknown. Overall, the effects of opioids appear to be modestly immunosuppressive.

Concentration – Efficacy Relationships

The minimum effective analgesic concentration will vary widely among patients, especially among patients who have been previously treated with opioid agonists. The minimum effective analgesic concentration of morphine for any individual patient may increase over time due to an increase in pain, the development of a new pain syndrome, and/or the development of analgesic tolerance [see Dosage and Administration (2.1, 2.5)].

Concentration – Adverse Reaction Relationships

There is a relationship between increasing morphine plasma concentration and increasing frequency of dose-related opioid adverse reactions such as nausea, vomiting, CNS effects, and respiratory depression. In opioid-tolerant patients, the situation may be altered by the development of tolerance to opioid-related adverse reactions [see Dosage and Administration (2.1, 2.2, 2.6)].

12.3 Pharmacokinetics

Intravenous Administration

Morphine has an apparent volume of distribution ranging from 1.0 to 4.7 L/kg after intravenous dosage. Protein binding is low, about 36%, and muscle tissue binding is reported as 54%. A blood-brain barrier exists, and when morphine is introduced outside of the CNS (e.g., intravenously), plasma concentrations of morphine remain higher than the corresponding CSF morphine levels. Conversely, when morphine is injected into the intrathecal space, it diffuses out into the systemic circulation slowly, accounting for the long duration of action of morphine administered by this route.

Morphine has a total plasma clearance which ranges from 0.9 to 1.2 L/kg/h (liters/kilogram/hour) in postoperative patients, but shows considerable interindividual variation. The major pathway of clearance is hepatic glucuronidation to morphine‑3‑glucuronide, which is pharmacologically inactive. The major excretion path of the conjugate is through the kidneys, with about 10% in the feces. Morphine is also eliminated by the kidneys, 2 to 12% being excreted unchanged in the urine. Terminal half-life is commonly reported to vary from 1.5 to 4.5 hours, although the longer half‑lives were obtained when morphine levels were monitored over protracted periods with very sensitive radioimmunoassay methods. The accepted elimination half-life in normal subjects is 1.5 to 2 hours.

Epidural Administration

Morphine, injected into the epidural space, is rapidly absorbed into the general circulation. Absorption is so rapid that the plasma concentration-time profiles closely resemble those obtained after intravenous or intramuscular administration. Peak plasma concentrations averaging 33–40 ng/mL (range 5–62 ng/mL) are achieved within 10 to 15 minutes after administration of 3 mg of morphine. Plasma concentrations decline in a multiexponential fashion. The terminal half-life is reported to range from 39 to 249 minutes (mean of 90 ± 34.3 min) and, though somewhat shorter, is similar in magnitude as values reported after intravenous and intramuscular administration (1.5–4.5 h). CSF concentrations of morphine, after epidural doses of 2 to 6 mg in postoperative patients, have been reported to be 50 to 250 times higher than corresponding plasma concentrations. The CSF levels of morphine exceed those in plasma after only 15 minutes and are detectable for as long as 20 hours after the injection of 2 mg of epidural morphine. Approximately 4% of the dose injected epidurally reaches the CSF. This corresponds to the relative minimum effective epidural and intrathecal doses of 5 mg and 0.25 mg, respectively. The disposition of morphine in the CSF follows a biphasic pattern, with an early half-life of 1.5 h and a late phase half-life of about 6 h. Morphine crosses the dura slowly, with an absorption half-life across the dura averaging 22 minutes. Maximum CSF concentrations are seen 60–90 minutes after injection. Minimum effective CSF concentrations for postoperative analgesia average 150 ng/mL (range < 1‑380 ng/mL).

Intrathecal Administration

The intrathecal route of administration circumvents meningeal diffusion barriers and, therefore, lower doses of morphine produce comparable analgesia to that induced by the epidural route. After intrathecal bolus injection of morphine, there is a rapid initial distribution phase lasting 15–30 minutes and a half-life in the CSF of 42–136 min (mean 90 ± 16 min). Derived from limited data, it appears that the disposition of morphine in the CSF, from 15 minutes postintrathecal administration to the end of a six-hour observation period, represents a combination of the distribution and elimination phases. Morphine concentrations in the CSF averaged 332 ± 137 ng/mL at 6 hours, following a bolus dose of 0.3 mg of morphine. The apparent volume of distribution of morphine in the intrathecal space is about 22 ± 8 mL.

Time-to-peak plasma concentrations, however, are similar (5-10 min) after either epidural or intrathecal bolus administration of morphine. Maximum plasma morphine concentrations after 0.3 mg intrathecal morphine have been reported from < 1 to 7.8 ng/mL.The minimum analgesic morphine plasma concentration during Patient‑Controlled Analgesia (PCA) has been reported as 20–40 ng/mL, suggesting that any analgesic contribution from systemic redistribution would be minimal after the first 30–60 minutes with epidural administration and virtually absent with intrathecal administration of morphine.

13 NONCLINICAL TOXICOLOGY

13.1 Carcinogenesis, Mutagenesis, Impairment of Fertility

Carcinogenesis

Long-term studies in animals to evaluate the carcinogenic potential of morphine have not been conducted.

Mutagenesis

No formal studies to assess the mutagenic potential of morphine have been conducted. In the published literature, morphine was found to be mutagenic in vitro increasing DNA fragmentation in human T-cells. Morphine was reported to be mutagenic in the in vivo mouse micronucleus assay and positive for the induction of chromosomal aberrations in mouse spermatids and murine lymphocytes. Mechanistic studies suggest that the in vivo clastogenic effects reported with morphine in mice may be related to increases in glucocorticoid levels produced by morphine in this species. In contrast to the above positive findings, in vitro studies in the literature have also shown that morphine did not induce chromosomal aberrations in human leukocytes or translocations or lethal mutations in Drosophila.

Impairment of Fertility

No formal nonclinical studies to assess the potential of morphine to impair fertility have been conducted.

Several nonclinical studies from the literature have demonstrated adverse effects on male fertility in the rat from exposure to morphine. One study in which male rats were administered morphine sulfate subcutaneously prior to mating (up to 30 mg/kg twice daily) and during mating (20 mg/kg twice daily) with untreated females, a number of adverse reproductive effects including reduction in total pregnancies and higher incidence of pseudopregnancies at 20 mg/kg/day (3.2 times the HDD) were reported.

Studies from the literature have also reported changes in hormonal levels in male rats (i.e., testosterone, luteinizing hormone) following treatment with morphine at 10 mg/kg/day or greater (1.6 times the HDD).

16 HOW SUPPLIED/STORAGE AND HANDLING

DURAMORPH (morphine sulfate injection, USP) is a preservative-free solution, available as 5 mg/10 mL (0.5 mg/mL) and 10 mg/10 mL (1 mg/mL), in amber ampuls, for single use administration.

NDC 0641-6020-10 5 mg/10 mL (0.5 mg/mL) Single Use amber ampuls packaged in 10s

NDC 0641-6019-10 10 mg/10 mL (1 mg/mL) Single Use amber ampuls packaged in 10s

DURAMORPH is supplied in sealed ampuls. Accidental dermal exposure should be treated by the removal of any contaminated clothing and rinsing the affected area with water.

PROTECT FROM LIGHT. Keep stored in carton until time of use. Store at 20˚‑25˚C (68˚‑77˚F), excursions permitted to 15˚‑30˚C (59˚‑86˚F) [See USP Controlled Room Temperature]. DO NOT FREEZE. DURAMORPH contains no preservative or antioxidant. Each 10 mL ampul of DURAMORPH is intended for SINGLE USE ONLY. Discard any unused portion. Do not heat-sterilize.

To report SUSPECTED ADVERSE REACTIONS, contact Hikma Pharmaceuticals USA Inc. at 1-877-845-0689, or the FDA at 1-800-FDA-1088 or www.fda.gov/medwatch.

For Product Inquiry call 1-877-845-0689.

17 PATIENT COUNSELING INFORMATION

Addiction, Abuse, and Misuse

Inform patients that the use of DURAMORPH, even when taken as recommended, can result in addiction, abuse, and misuse, which can lead to overdose and death [see Warnings and Precautions (5.2)].

Life-Threatening Respiratory Depression

Inform patients of the risk of life-threatening respiratory depression, including information that the risk is greatest when starting DURAMORPH or when the dosage is increased, and that it can occur even at recommended dosages [see Warnings and Precautions (5.3)].

Hyperalgesia and Allodynia

Advise patients to inform their healthcare provider if they experience symptoms of hyperalgesia, including worsening pain, increased sensitivity to pain, or new pain [see Warnings and Precautions (5.8), Adverse Reactions (6)].

Serotonin Syndrome

Inform patients that opioids could cause a rare but potentially life-threatening condition called serotonin syndrome resulting from concomitant administration of serotonergic drugs. Warn patients of thesymptoms of serotonin syndrome and to seek medical attention right away if symptoms develop after discharge from the hospital. Instruct patients to inform their physicians if they are taking, or plan to take serotonergic medications [see Drug Interactions (7)].

Constipation

Advise patients of the potential for severe constipation, including management instructions and when to seek medical attention [see Adverse Reactions (6), Clinical Pharmacology (12.2)].

Manufactured by:
Hikma Pharmaceuticals USA Inc.
Berkeley Heights, NJ 07922

462-212-08

PRINCIPAL DISPLAY PANEL

NDC 0641-6020-01 10 mL Ampul
Rx only
Duramorph
(Morphine Sulfate Injection, USP) CII
5 mg per 10 mL
(0.5 mg/mL)
Preservative Free
For Intravenous, Epidural, or Intrathecal Use

NDC 0641-6020-10
Rx only
Duramorph
(Morphine Sulfate Injection, USP) CII
5 mg per 10 mL
(0.5 mg/mL)
Preservative Free
For Intravenous, Epidural, or Intrathecal Use
10 x 10 mL Ampuls

PRINCIPAL DISPLAY PANEL

NDC 0641-6019-01 10 mL Ampul
Rx only
Duramorph
(Morphine Sulfate Injection, USP) CII
10 mg per 10 mL
(1 mg/mL)
Preservative Free
For Intravenous, Epidural, or Intrathecal Use

NDC 0641-6019-10
Rx only
Duramorph
(Morphine Sulfate Injection, USP) CII
10 mg per 10 mL
(1 mg/mL)
Preservative Free
For Intravenous, Epidural, or Intrathecal Use
10 x 10 mL Ampuls